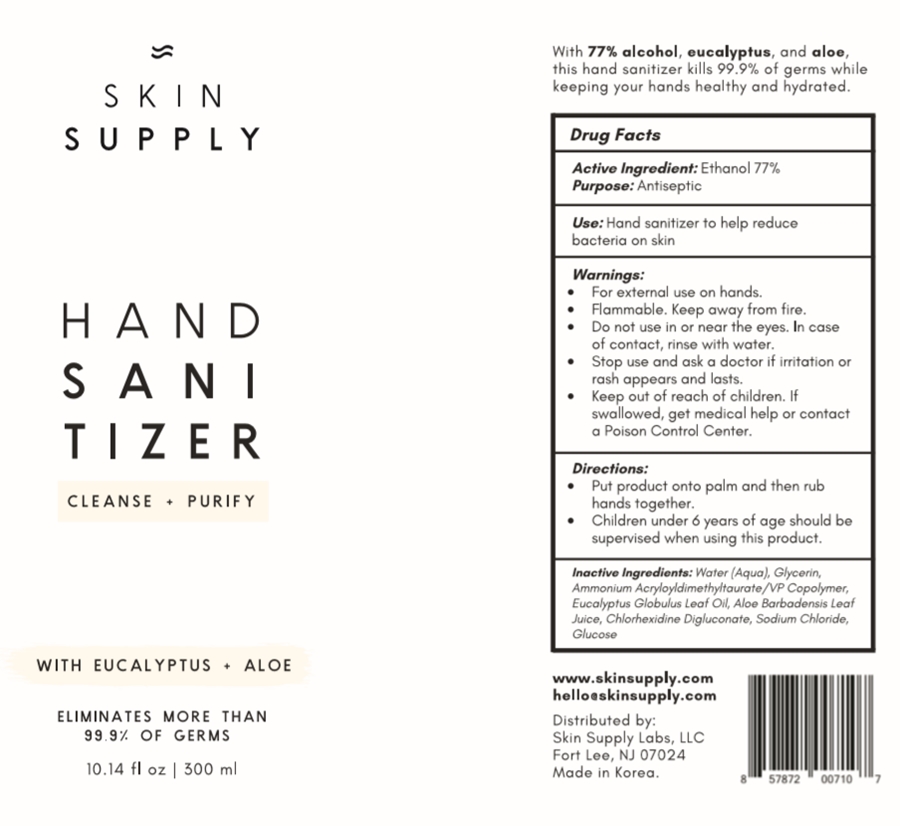 DRUG LABEL: SKIN SUPPLY HAND SANITIZER
NDC: 76731-202 | Form: LIQUID
Manufacturer: BBHC CO., LTD
Category: otc | Type: HUMAN OTC DRUG LABEL
Date: 20200425

ACTIVE INGREDIENTS: ALCOHOL 77 mL/100 mL
INACTIVE INGREDIENTS: AMMONIUM ACRYLOYLDIMETHYLTAURATE 0.6 mL/100 mL; EUCALYPTUS OIL 0.5 mL/100 mL; WATER 18.38 mL/100 mL; GLYCERIN 3 mL/100 mL; SODIUM CHLORIDE 0.005 mL/100 mL; ANHYDROUS DEXTROSE 0.005 mL/100 mL; ALOE VERA LEAF 0.5 mL/100 mL; CHLORHEXIDINE GLUCONATE 0.01 mL/100 mL

Active Ingredient

Ethanol 77%

Purpose

Antiseptic

Use

Hand sanitizer to help reduce bacteria on skin

Warnings

For external use on hands.

Flammable. Keep away from fire.

Warnings

Do not use in or near the eyes. In case of contact, rinse with water.

Warnings

Stop use and ask a doctor if irritation or rash appears and lasts.

Warnings

Keep out of reach of children. If swallowed, get medical help or contact a Poison Control Center.

Directions

Put product onto palm and then rub hands together.

Children under 6 years of age should be supervised when using this product.

Inactive Ingredients

Water, Glycerin, Ammonium Acryloyldimethyltaurate/VP Copolymer, Eucalyptus Globulus Leaf Oil, Aloe Barbadensis Leaf Juice, Chlorhexidine Digluconate, Sodium Chloride, Glucose